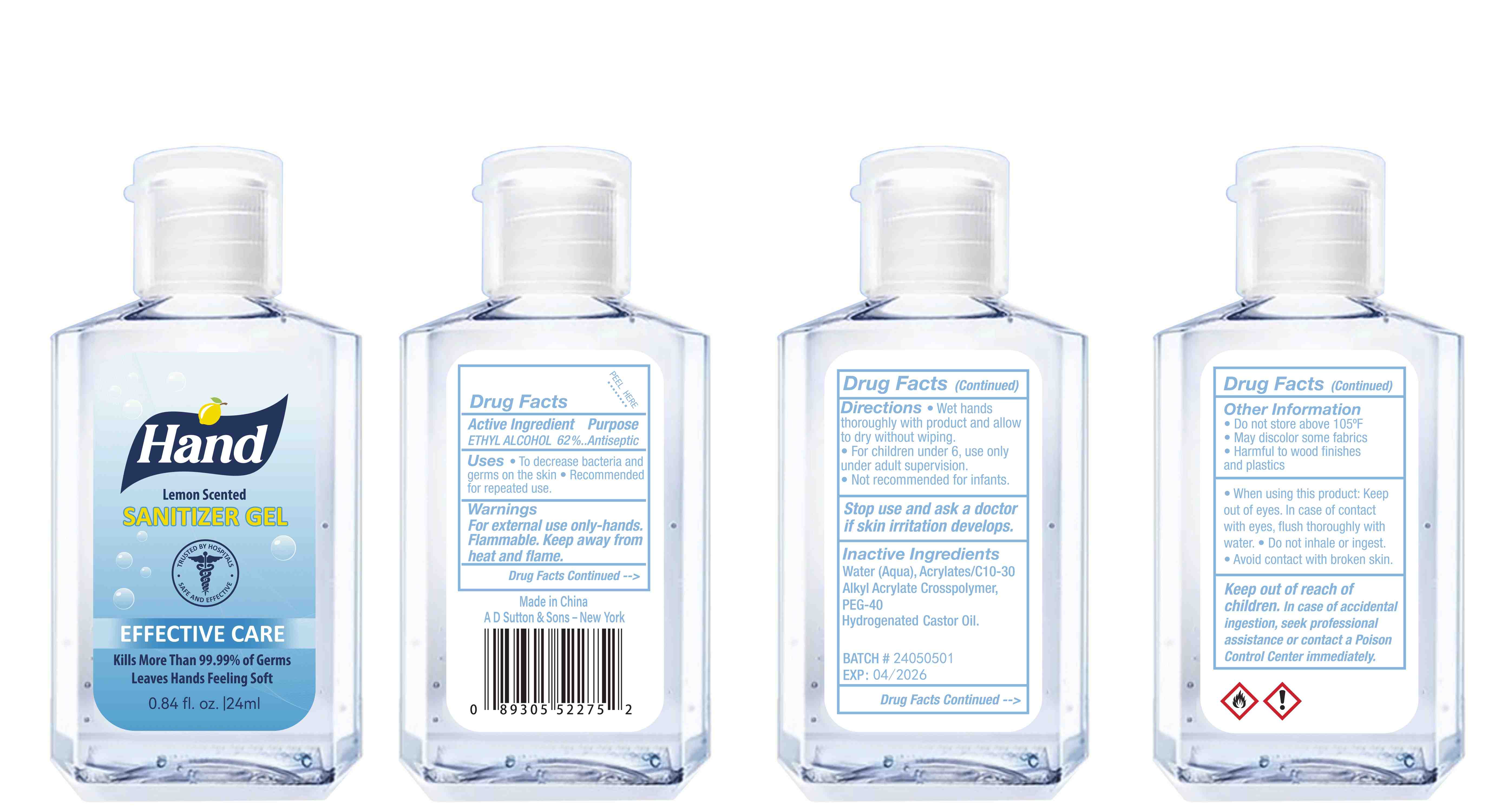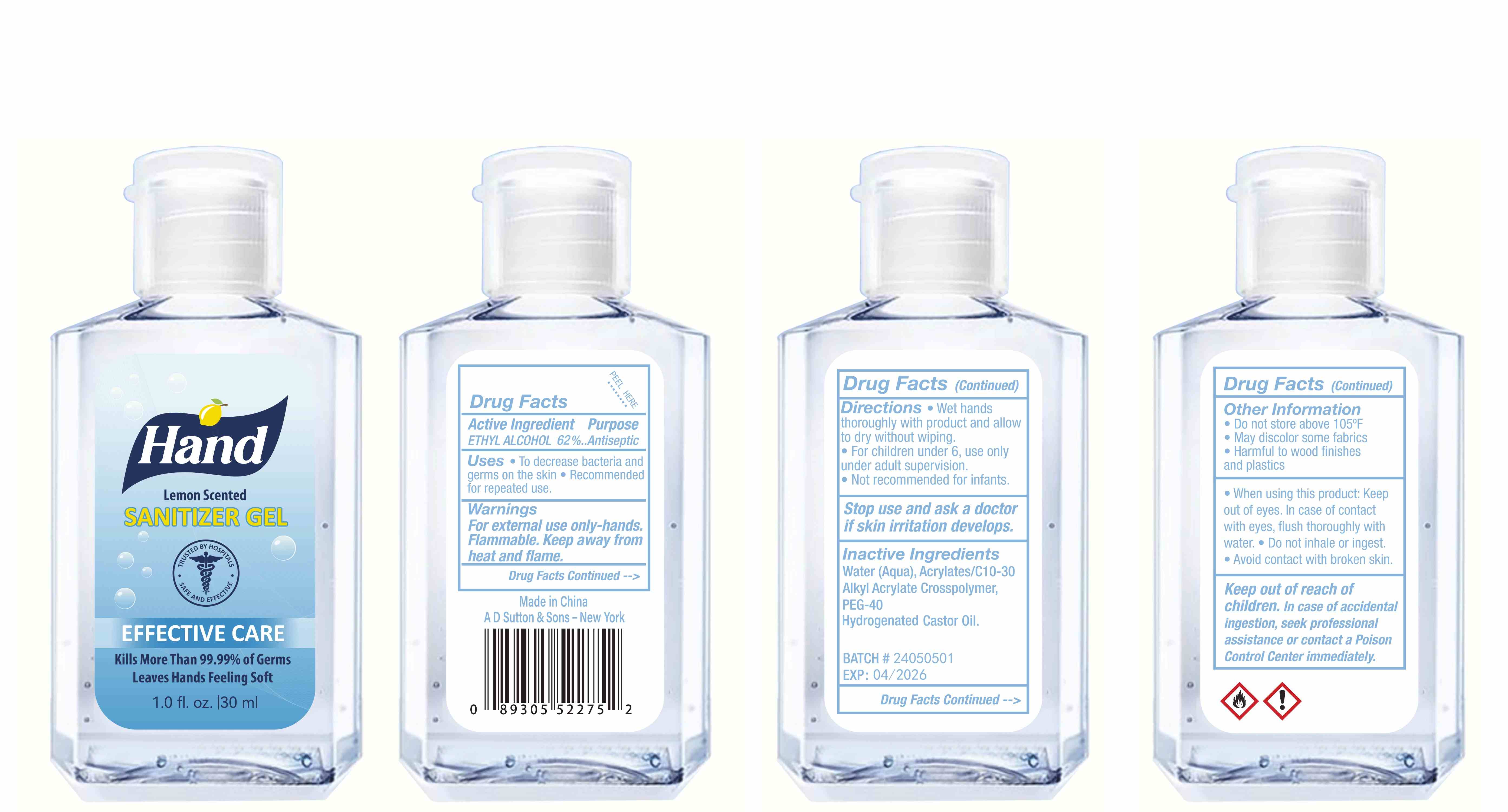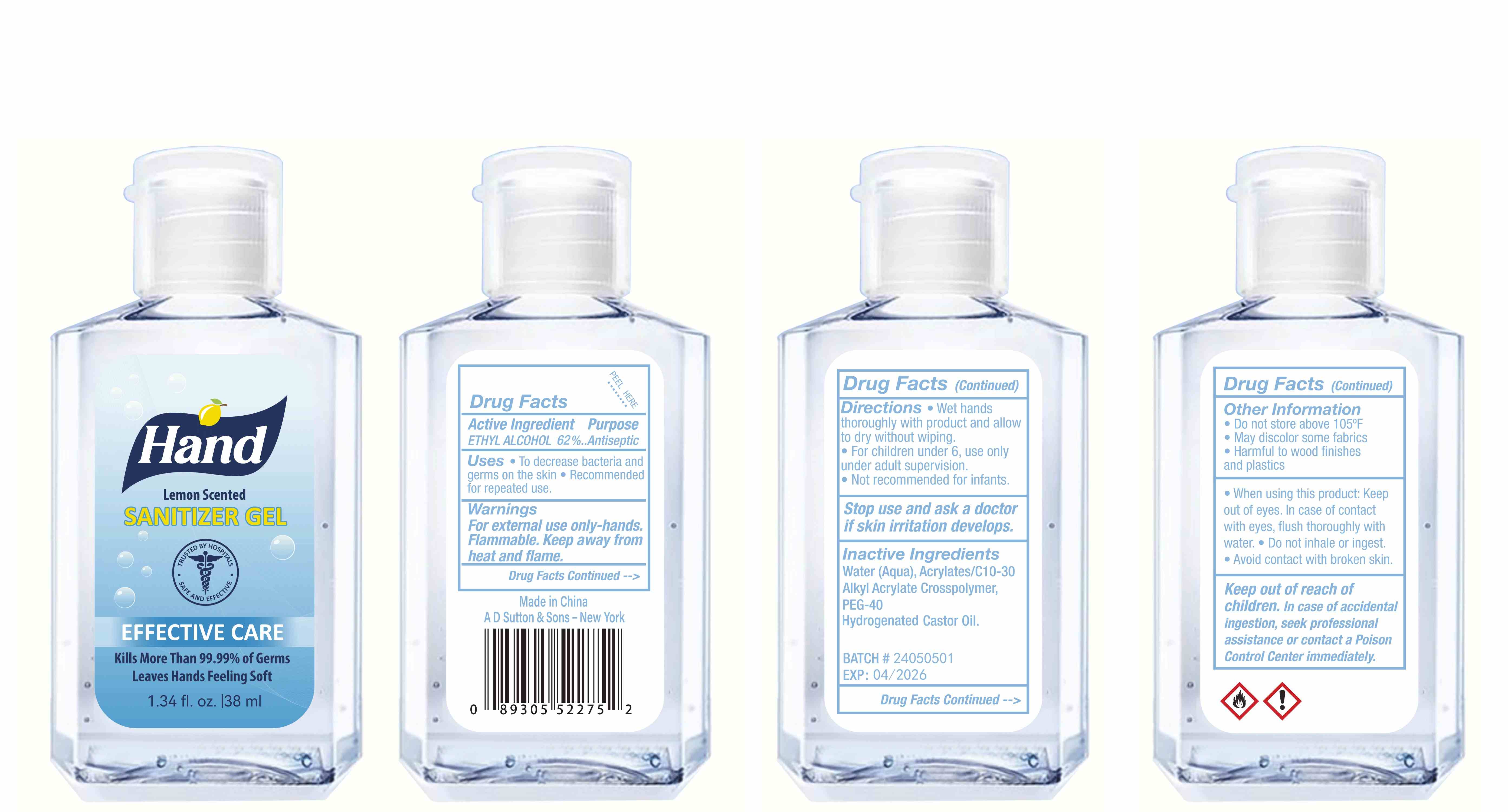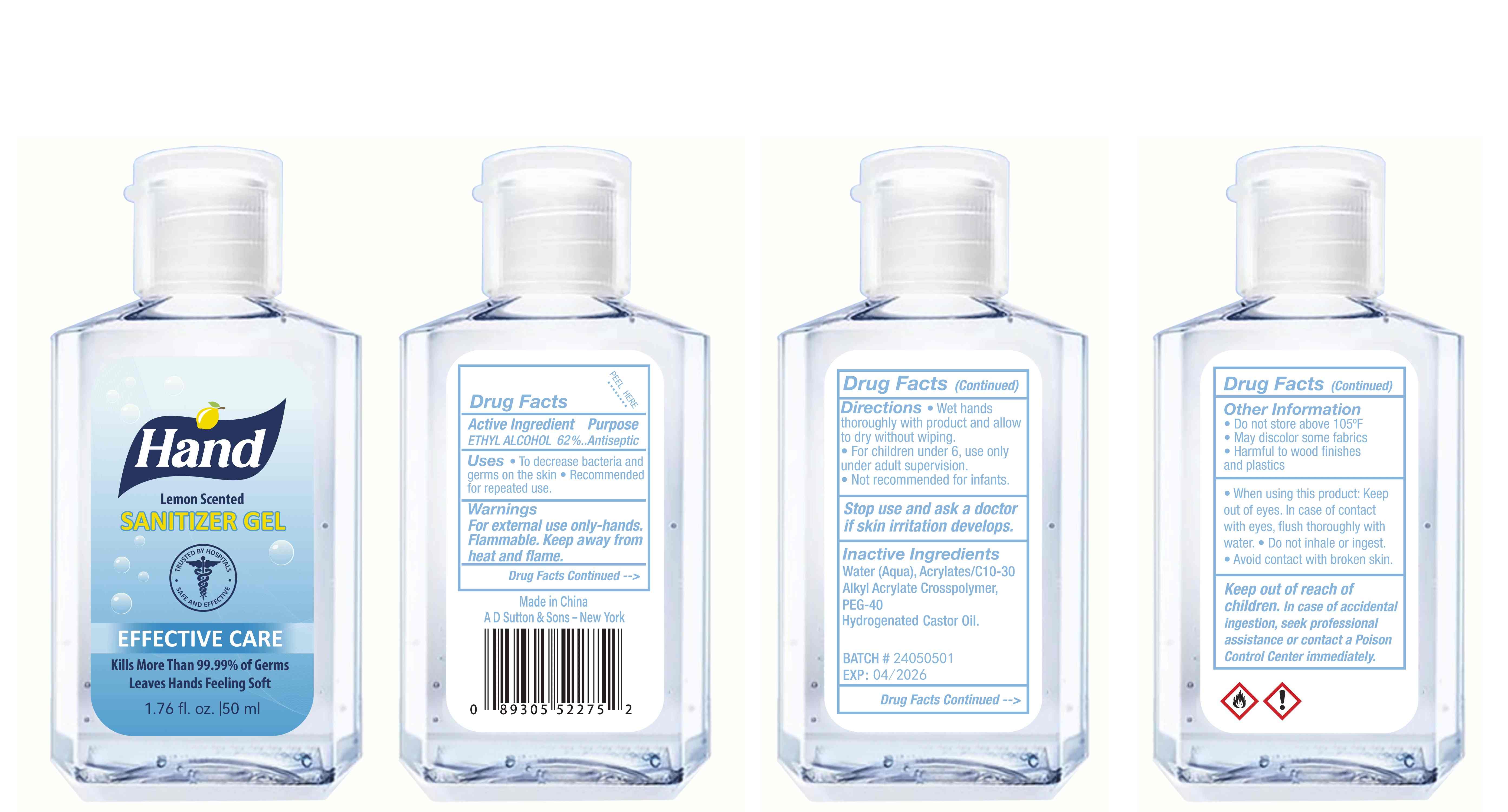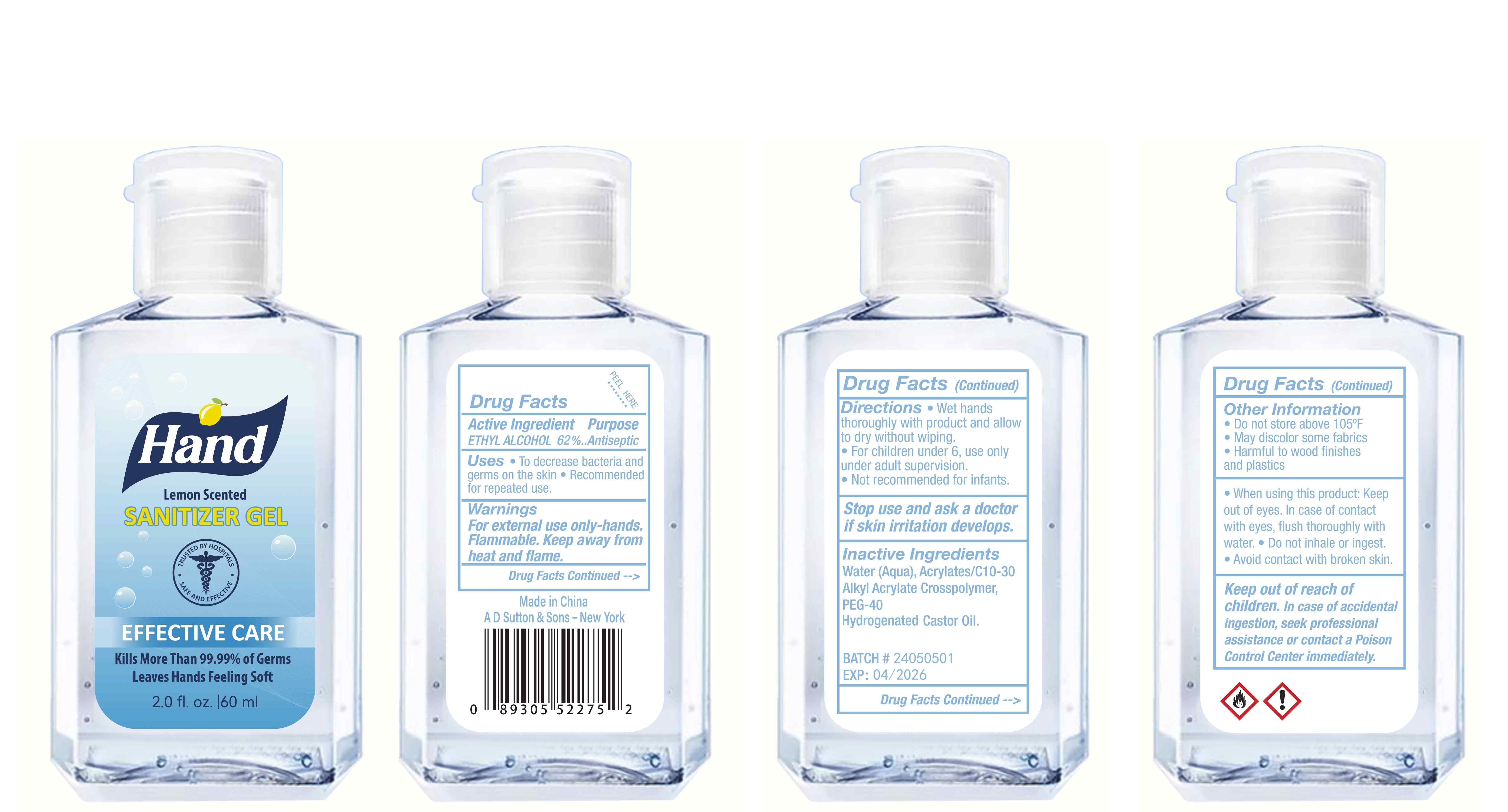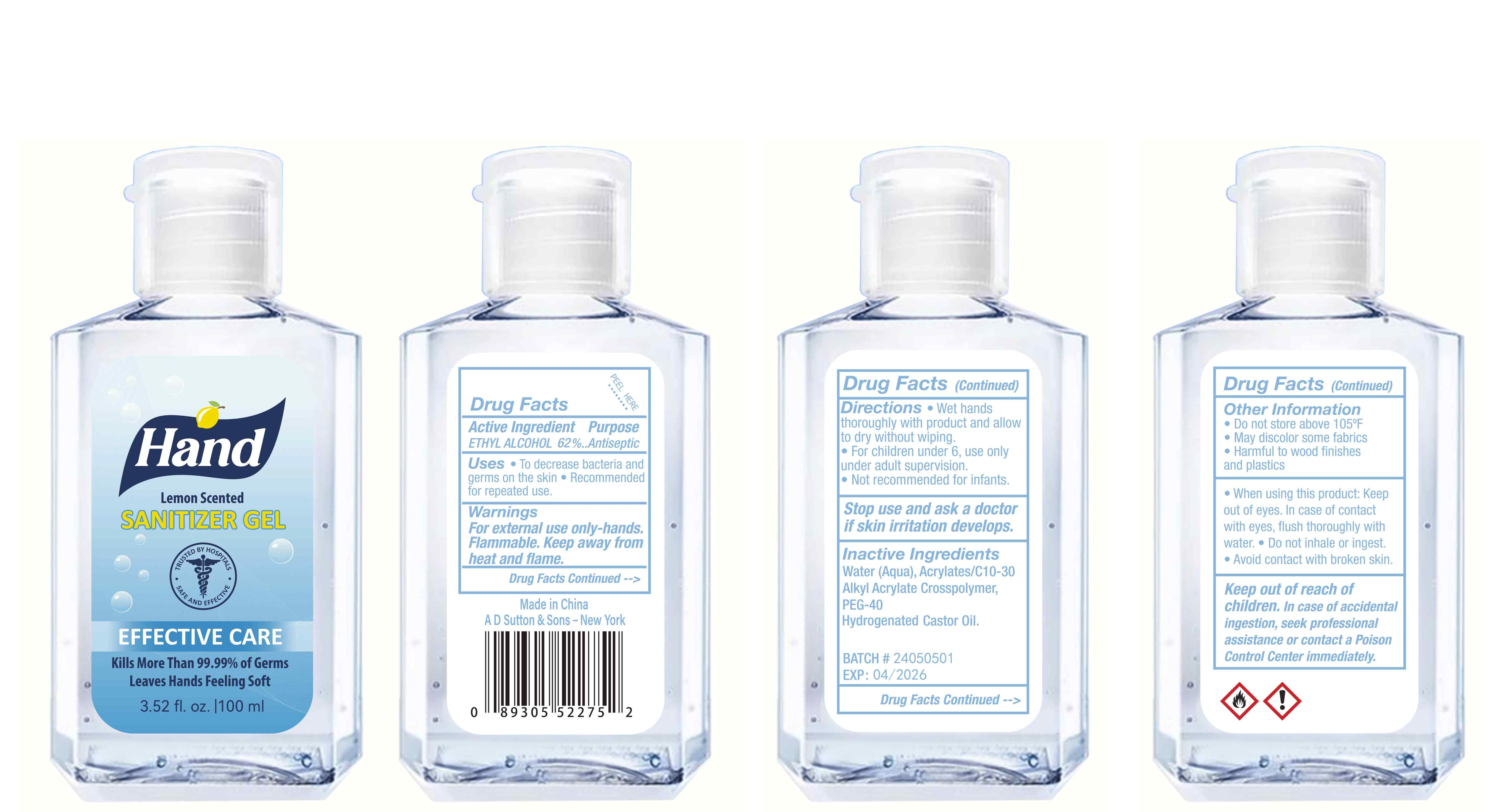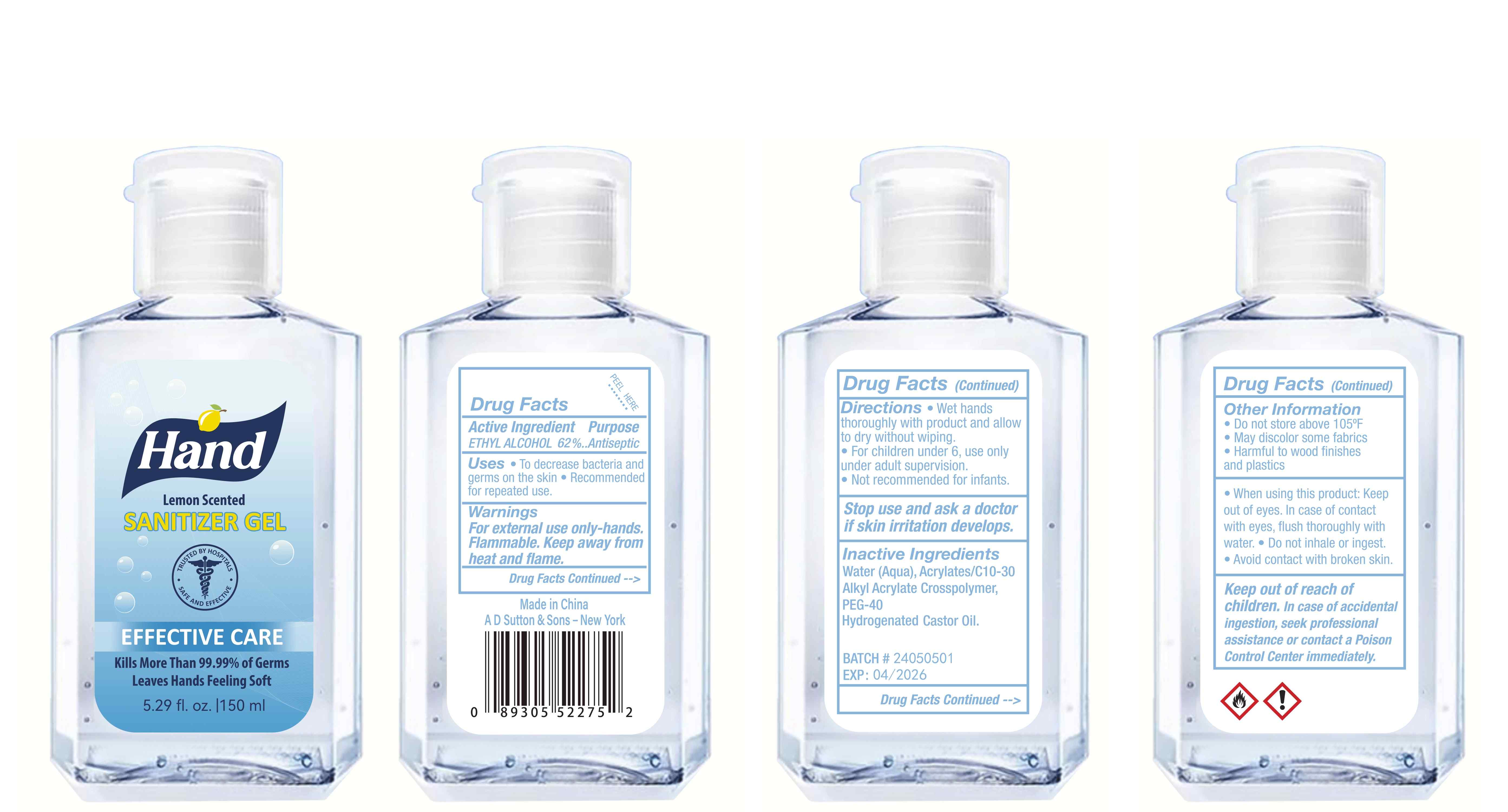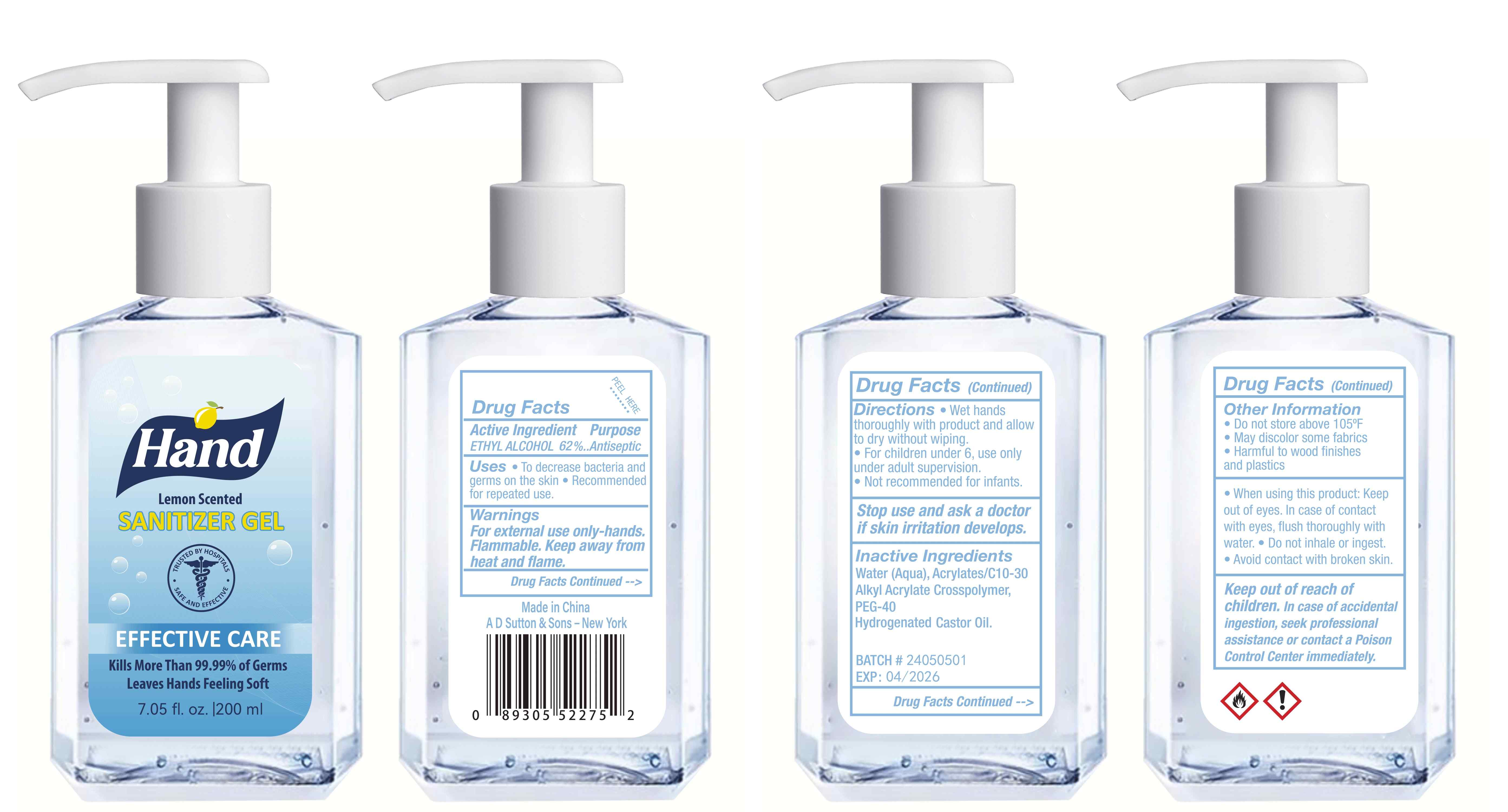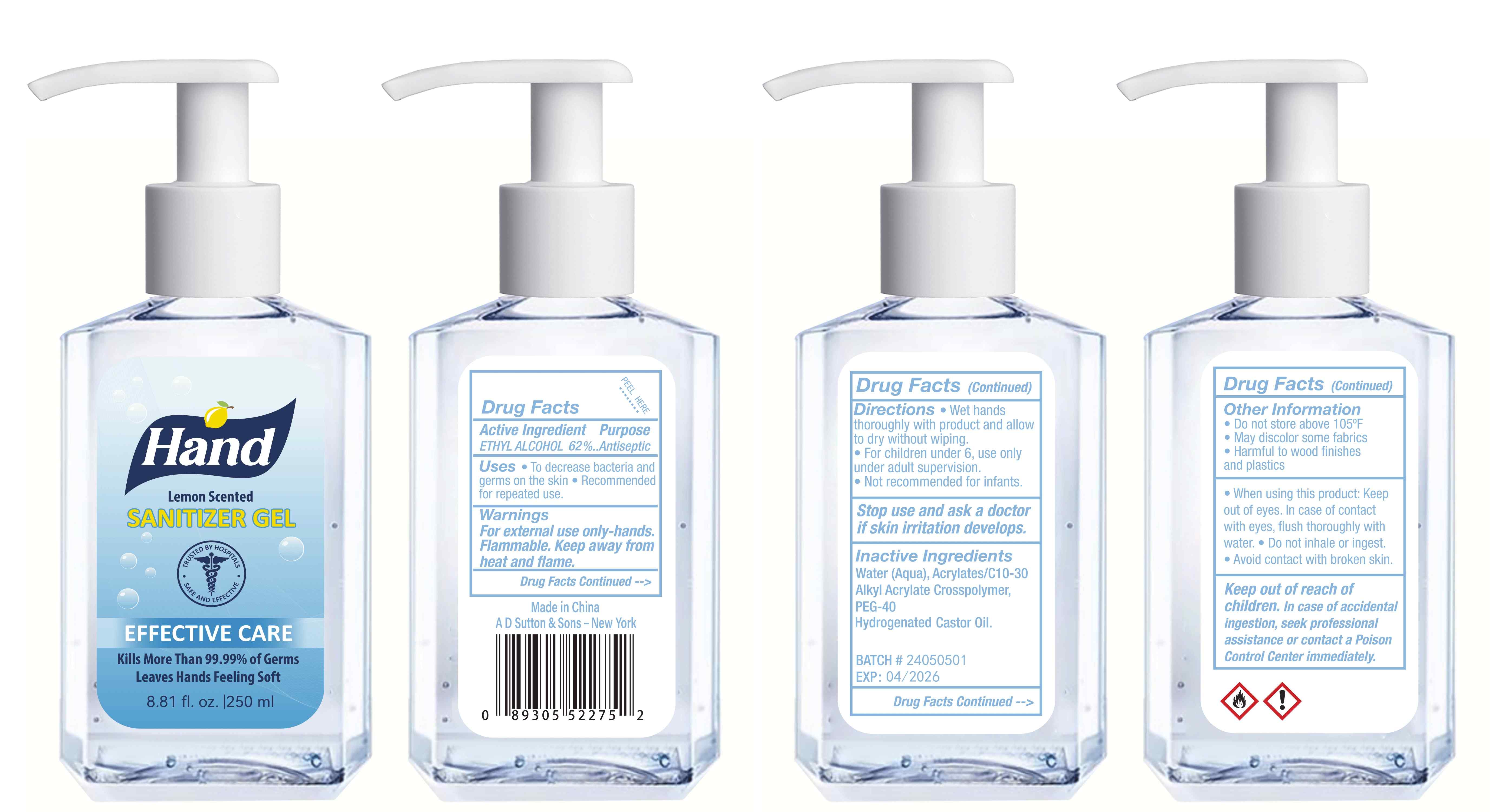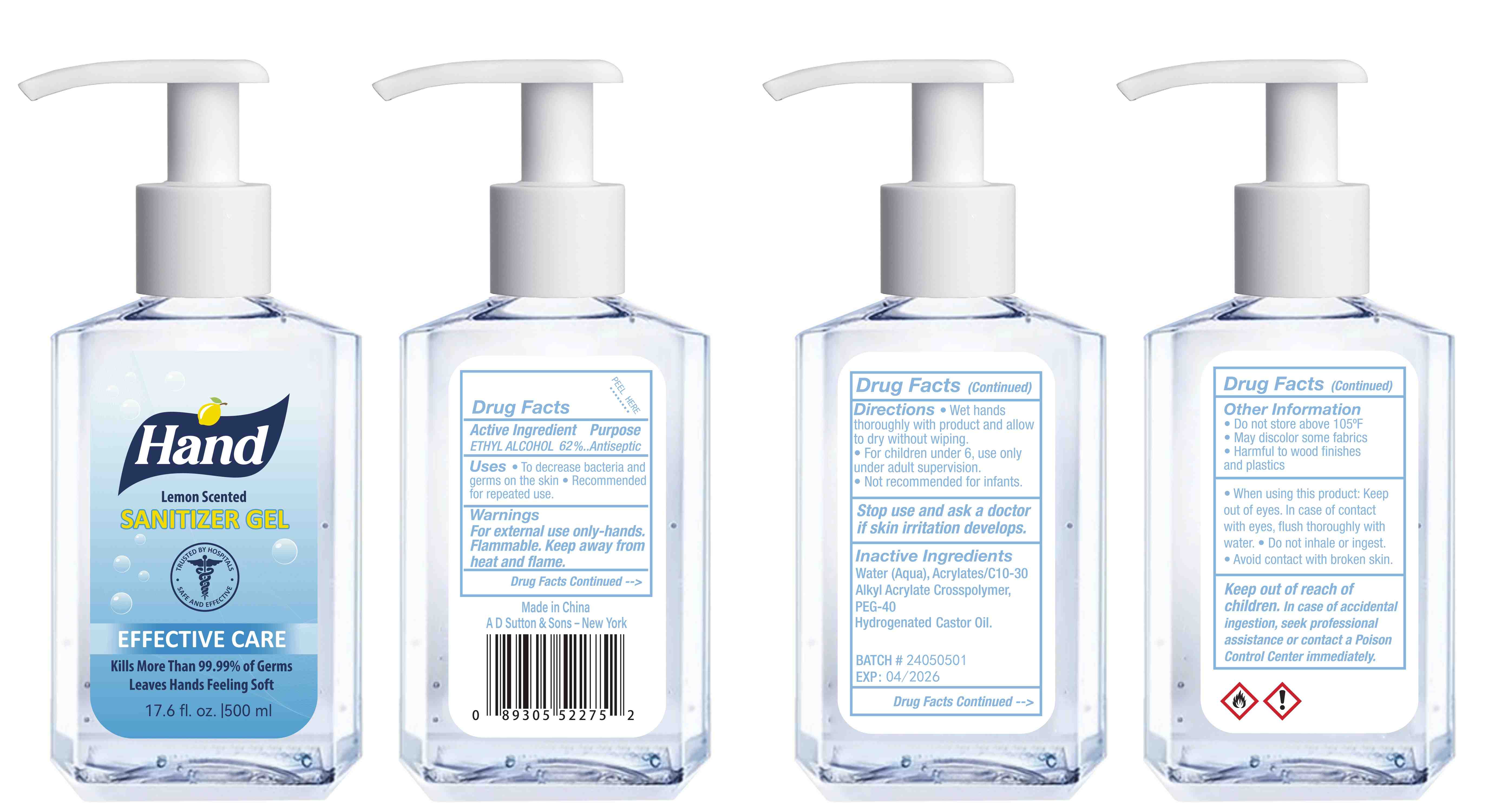 DRUG LABEL: Hand Sanitizer
NDC: 77975-015 | Form: GEL
Manufacturer: Guangzhou Tingcai Cosmetic Co., Ltd.
Category: otc | Type: HUMAN OTC DRUG LABEL
Date: 20240306

ACTIVE INGREDIENTS: ALCOHOL 62 mL/100 mL
INACTIVE INGREDIENTS: WATER; ACRYLATES/C10-30 ALKYL ACRYLATE CROSSPOLYMER (60000 MPA.S); PEG-40 CASTOR OIL; LEMON PEEL

77975-015 Hand Sanitizer

Active Ingredient(s)

ETHYL ALCOHOL 62%

Purpose

Antiseptic

Use

Uses To decrease bacteria andgerms on the skin Recommended for repeated use.

Warnings

For external use only.

Flammable. Keep away from heat or flame.

Do not use

In children less than 2 months of age.

When using this product Keep out of eyes, ears, and mouth. In case of contact with eyes, rinse eyes throughly with water.

Stop use and ask a doctor if irritation or rash occurs. These may be sians of a serious condition.

KEEP OUT OF REACH OF CHILDREN

Keep out of reach of chlldren. If swallowed. get medical help or contact a Polson Control center right away.

Directions

WET HANS THOROUGHLY WITH PRODUCT AND ALLOW TO DRY WITHOUT WIPING

FOR children under , use only under adult supervision

Not recommedned for infants

Other information

Do not store above 105℉FMay discolor some fabricsHarmful to wood finishesand plastics

When using this product: Keepout of eyes. Iin case of contactwith eyes, flush thoroughly withwater. e Do not inhale or ingest.Avoid contact with broken skin.

Inactive ingredients

Water (Aqua), Acrylates/C10-30Alkyl Acrylate Crosspolymer,PEG-40Hydrogenated Castor 0il.